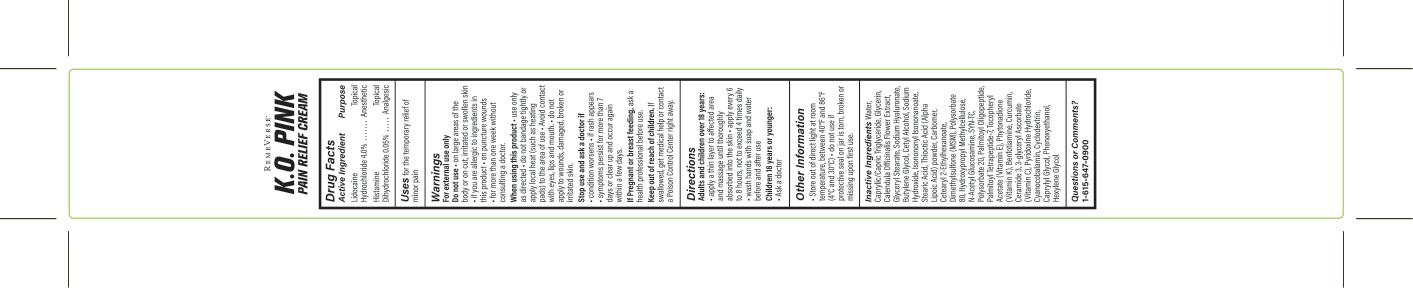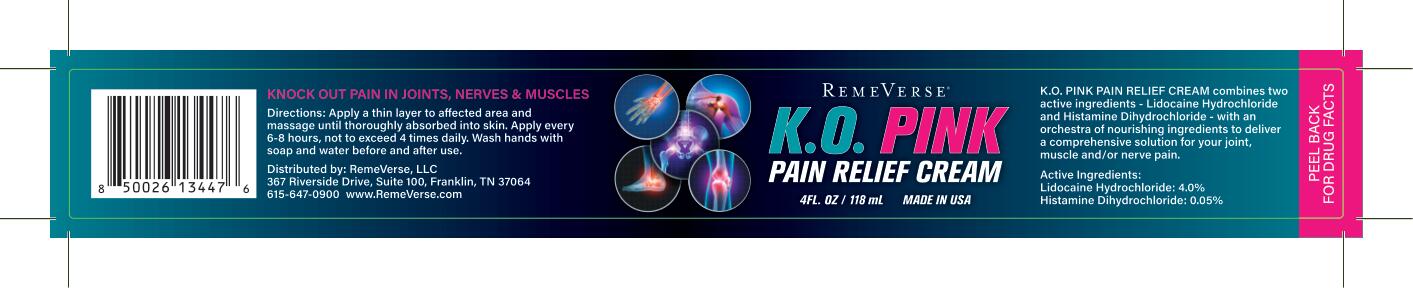 DRUG LABEL: KO Pink Pain Relief Cream
NDC: 70317-005 | Form: CREAM
Manufacturer: Remeverse
Category: otc | Type: HUMAN OTC DRUG LABEL
Date: 20241216

ACTIVE INGREDIENTS: LIDOCAINE HYDROCHLORIDE 0.04 g/1 mL; PHENOLATE SODIUM 0.005 g/1 mL
INACTIVE INGREDIENTS: PALMITOYL TRIPEPTIDE-1; DIMETHYL SULFONE; BUTYLENE GLYCOL; CETYL ALCOHOL; CETEARYL ETHYLHEXANOATE; CYCLODEXTRINS; HYALURONATE SODIUM; GLYCERIN; THIOCTIC ACID; N-ACETYLGLUCOSAMINE; CERAMIDE 3; CAPRYLYL GLYCOL; CALENDULA OFFICINALIS FLOWER; GLYCERYL 1-STEARATE; SODIUM HYDROXIDE; STEARIC ACID; POLYSORBATE 80; .ALPHA.-TOCOPHEROL ACETATE, DL-; CYANOCOBALAMIN; TETRADECYL AMINOBUTYROYLVALYLAMINOBUTYRIC UREA TRIFLUOROACETATE; POLYSORBATE 20; PALMITOYL TETRAPEPTIDE-7; BENFOTIAMINE; PYRIDOXINE HYDROCHLORIDE; PALMITOYLLYSYLVALYLDIAMINOBUTYROYLTHREONINE; PHENOXYETHANOL; PHYTONADIONE; HYPROMELLOSE, UNSPECIFIED; CARBOMER HOMOPOLYMER, UNSPECIFIED TYPE; WATER; CURCUMIN; 3-GLYCERYL ASCORBATE; HEXYLENE GLYCOL; MEDIUM-CHAIN TRIGLYCERIDES; ISONONYL ISONONANOATE; PALMITOYL TRIPEPTIDE-5

KO Pink Pain Relief Cream

Active Ingredients

Lidocaine Hydrochloride 4.0%

Phenolate Sodium 0.5%

Inactive Ingredients

Water, Caprylic/Capric Triglyceride, Glycerin, Calendula Officinalis Flower Extract, Glyceryl Stearate, Sodium Hyaluronate, Butylene Glycol, Cetyl Alcohol, Sodium Hydroxide, Isonononyl Isononanoate, Stearic Acid, Thioctic Acid (Alpha Lipoic Acid) powder, Carbomer, Cetearyl 2-Ethylhexanoate, Dimethylsulfone (MSM), Polysorbate 80, Hydroxypropyl Methylcellulose, N-Acetyl Glucosamine, SYN-TC, Polysorbate 20, Palmitoyl Oligopeptide, Palmitoyl Tetrapeptide-7, Tocopheryl Acetate (Vitamin E), Phytonadione (Vitamin K), Benfotiamine, Curcumin, Ceramide 3, 3-glyceryl Ascorbate (Vitamin C), Pyridoxine Hydrochloride, Cyanocobalamin, Cyclodextrin, Caprylyl Glycol, Phenoxyethanol, Hexylene Glycol

Directions

Adults and children over 18 years:

- apply a thin layer to affected area and massage until thoroughly absorbed into the skin
- apply every 6 to 8 hours, not to exceed 4 times daily
- wash hands with soap and water before and after use

Children 18 years or younger:

- Ask a doctor

Use

For the temporary relief of minor pain

Stop Use

Stop use and ask a doctor if

- condition worsens
- if rash appears
- symptoms persist for more than 7 days or clear up and occur again within a few days

Warning - Keep out of reach of children

If swallowed, get medical help or contact a Poison Control Center right away.

Warnings

For external use only

Do not use:

- In large quantities
- Over raw surfaces or blistered areas
- if you are allergic to ingredients in this product
- on puncture wounds
- Over large areas of the body

When using this product:

- use only as directed
- do not bandage tightly or apply local heat (such as heating pads) to the area of use
- avoid contact with eyes, lips and mouth
- do not apply to wounds, damaged, broken or irritated skin

Storage

store out of direct light at room temperature, between 40F and 86F (4C and 30C)

do not use if protective seal on jar is torn broken or missing upon first use

Purpose

For the relief of minor pain

Pregnant or Breastfeeding

If pregnant or breast feeding:

Ask a health professional before use